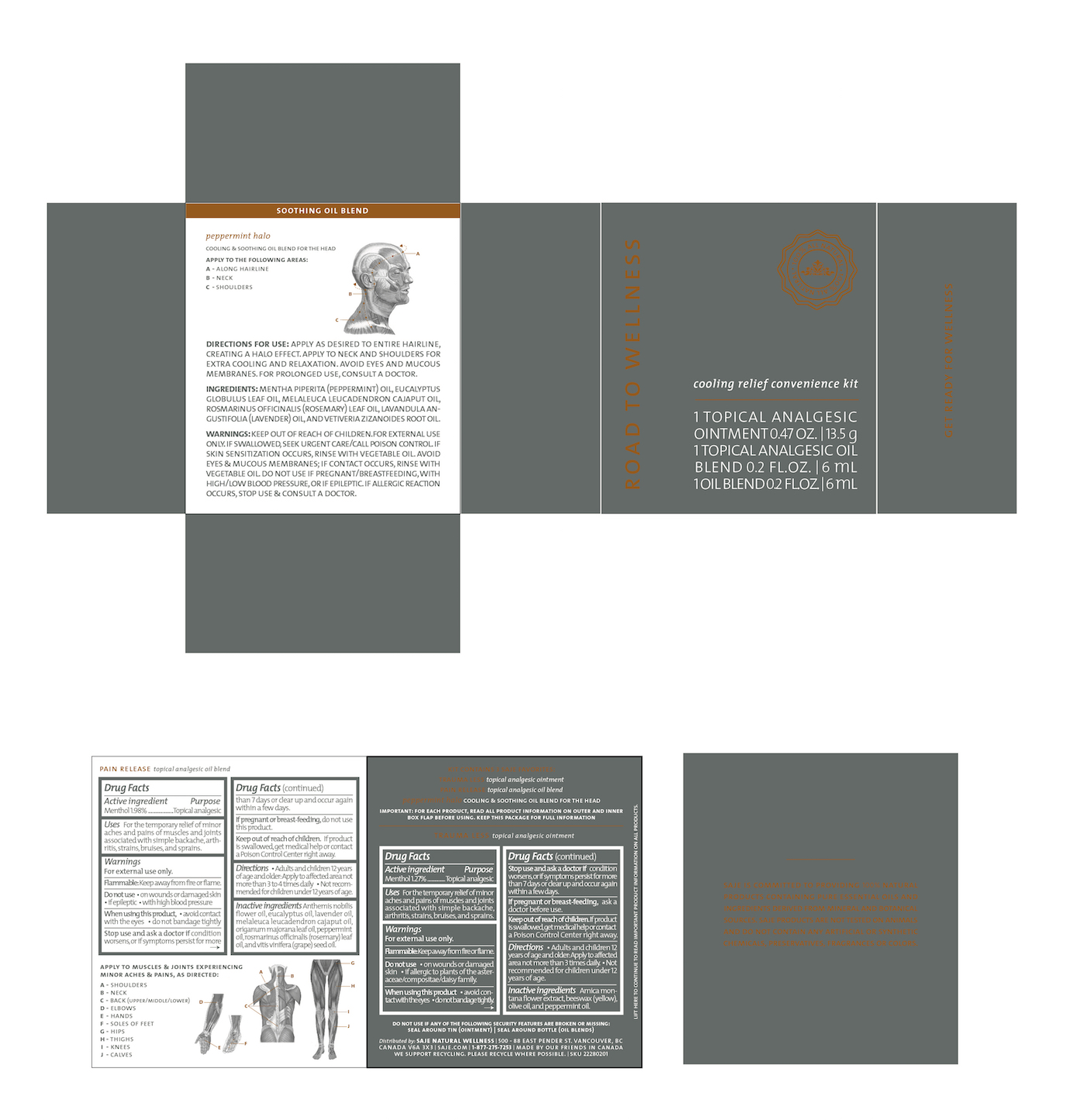 DRUG LABEL: Road to Wellness
NDC: 70983-017 | Form: KIT | Route: TOPICAL
Manufacturer: Saje Natural Business Inc.
Category: otc | Type: HUMAN OTC DRUG LABEL
Date: 20161011

ACTIVE INGREDIENTS: MENTHOL 12.7 mg/1 g; MENTHOL 17.62 mg/1 mL
INACTIVE INGREDIENTS: ARNICA MONTANA FLOWER; YELLOW WAX; OLIVE OIL; PEPPERMINT OIL; CHAMAEMELUM NOBILE FLOWER OIL; EUCALYPTUS OIL; LAVENDER OIL; CAJUPUT OIL; SWEET MARJORAM OIL; PEPPERMINT OIL; ROSEMARY OIL; GRAPE SEED OIL

Road to Wellness Cooling Relief Convenience Kit (13.5 g, 2 x 6 ml)

Kit Contains 3 SAJE FAVORITES:

TRAUMA LESS topical analgesic ointment

PAIN RELEASE topical analgesic oil blend

peppermint halo COOLING & SOOTHING OIL BLEND FOR THE HEAD

IMPORTANT: FOR EACH PRODUCT, READ ALL PRODUCT INFORMATION ON OUTER AND INNER BOX FLAP BEFORE USING. KEEP THIS PACKAGE FOR FULL INFORMATION.

DO NOT USE IF THE FOLLOWING SECURITY FEATURES ARE BROKEN OR MISSING:

SEAL AROUND TIN (OINTMENT) | SEAL AROUND BOTTLE (OIL BLENDS)

Distributed by: SAJE NATURAL WELLNESS | 500-88 E. Pender St. Vancouver, BC Canada V6A 3X3 | saje.com | 1-877-275-7253 | Made by our friends in Canada

We support recycling. Please recycle where possible

SKU 22280201

LIFT HERE TO CONTINUE TO READ IMPORTANT PRODUCT INFORMATION ON ALL PRODUCTS.

GET READY FOR WELLNESS

Drug Facts Active ingredient

Menthol 1.27%

Purpose Topical analgesic

Uses For the temporary relief of minor aches and pains of muscles and joints associated with simple backache, arthritis, strains, bruises, and sprains.

Warnings

For external use only.

Flammable. Keep away from fire or flame.

Do not use

- on wounds or damaged skin
- if allergic to plants of the asteraceae/compositae/daisy family.

When using this product

- avoid contact with the eyes
- do not bandage tightly.

Stop use and ask a doctor

if condition worsens, or if symptoms persist for more than 7 days or clear up and occur again within a few days.

If pregnant or breast-feeding,

ask a doctor before use.

Keep out of reach of children.

If product is swallowed, get medical help or contact a Poison Control Center right away.

Directions

- Adults and children 12 years of age and older: Apply to affected area

DOSAGE AND ADMINISTRATION

not more than 3 times daily.

- Not recommended for children under 12 years of age.

Inactive ingredients

Arnica montana flower extract, beeswax (yellow), olive oil, and peppermint oil.

PAIN RELEASE - topical analgesic oil blend Drug Facts Active ingredient

Menthol 1.98%

Purpose Topical Analgesic

Uses For the temporary relief of minor aches and pains of muscles and joints associated with simple backache, arthritis, strains, bruises, and sprains

Warnings

For external use only.

Flammable. Keep away from fire or flame.

Do not use

- on wounds or damaged skin
- if epileptic
- with high blood pressure

When using this product,

- avoid contact with the eyes
- do not bandage tightly

Stop use and ask a doctor if

condition worsens, or if symptoms persist for more than 7 days or clear up and occur again within a few days.

If pregnant or breast-feeding,

do not use this product

Keep out of reach of children.

If product is swallowed, get medical help or contact a Poison Control Center right away.

Directions

- Adults and children 12 years of age and older: Apply to affected area

DOSAGE AND ADMINISTRATION

not more than 3 to 4 times daily

- Not recommended for children under 12 years of age

Inactive ingredients

Anthemis nobilis flower oil, eucalyptus oil, lavender oil, melaleuca leucadendron cajaput oil, origanum majorana leaf oil, peppermint oil, rosmarinus officinalis (rosemary) leaf oil, and vitis vinifera (grape) seed oil.

Pain Release - topical analgesic oil blend

Apply to muscles & joints experiencing minor aches & pains, as directed:

A - Shoulders

B - Neck

C - Back (upper/middle/lower)

D - Elbows

E - Hands

F - Soles of Feet

G - Hips

H - Thighs

I - Knees

J - Calves

SOOTHING OIL BLEND peppermint halo COOLING & SOOTHING OIL BLEND FOR THE HEAD

Apply to the following areas:

A - Along hairline

B - Neck

C - Shoulders

Directions for use: Apply as desired to entire hairline, creating a halo effect. Apply to neck and shoulders for extra cooling and relaxation. Avoid eyes and mucous membranes. For prolonged use, consult a doctor.

Ingredients: Mentha piperita (peppermint) oil, eucalyptus globulus leaf oil, melaleuca leucadendron cajaput oil, rosmarinus officinalis (rosemary) leaf oil, lavandula angustifolia (lavender) oil, and vetiveria zizanoides root oil.

Warnings:

- Keep out of reach of children.
- For external use only. if swallowed, seek urgent care/call poison control.
- If skin sensitization occurs, rinse with vegetable oil.
- Avoid eyes & mucous membranes; if contact occurs, rinse with vegetable oil.
- Do not use if pregnant/breastfeeding, with high/low blood pressure, or if epileptic.
- If allergic reaction occurs, stop use & consult a doctor.

Saje is committed to providing 100% natural products containing pure essential oils and ingredients derived from mineral and botanical sources. Saje products are not tested on animals and do not contain any artificial or synthetic chemicals, preservatives, fragrances or colors.

PACKAGE LABEL

ROAD TO WELLNESS

cooling relief convenience kit

1 TOPICAL ANALGESIC OINTMENT 0.47 OZ. | 13.5 g

1 TOPICAL ANALGESIC OIL BLEND 0.2 FL.OZ. | 6 mL

1 OIL BLEND 0.2 FL.OZ. | 6 mL